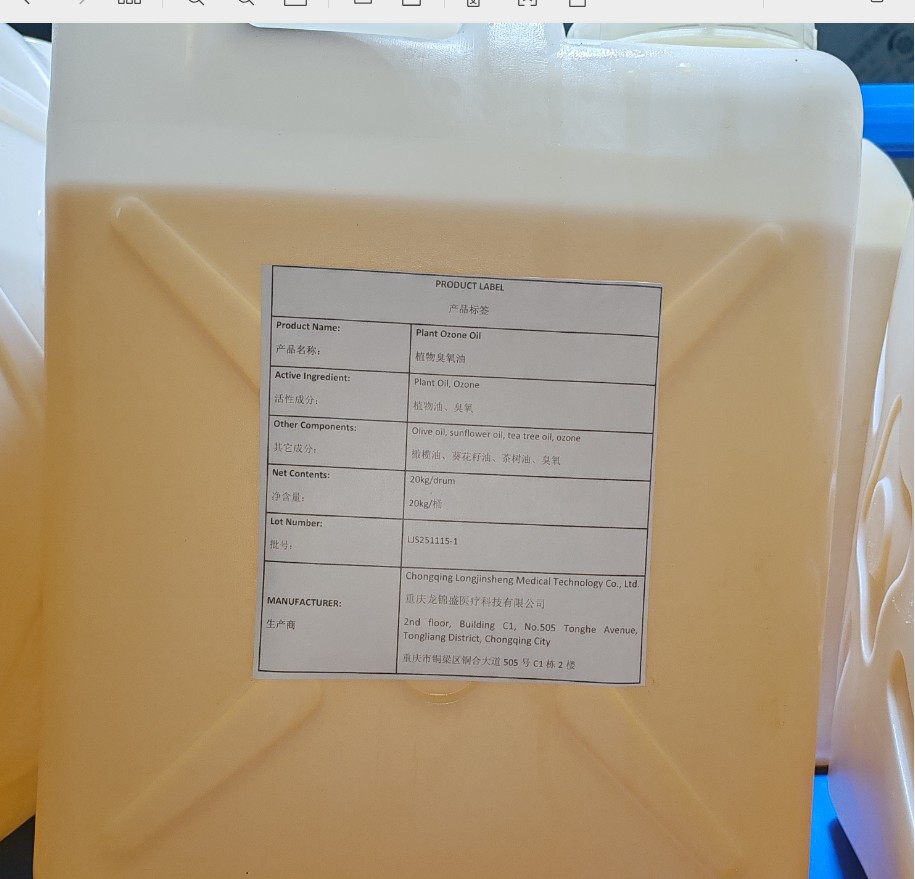 DRUG LABEL: Plant Ozone Oil
NDC: 87317-003 | Form: LIQUID
Manufacturer: Chongqing Longjinsheng Medical Technology Co., Ltd.
Category: otc | Type: HUMAN OTC DRUG LABEL
Date: 20260119

ACTIVE INGREDIENTS: OZONE 1 kg/100 kg
INACTIVE INGREDIENTS: SUNFLOWER OIL

87317-003

Active Ingredient

Ozone 1%

Purpose

It can reduce and kill bacteria, fungi, and certain viruses.

Use

Use after cleansing the skin.

Warnings

For medical use only. Keep out of reach of children.

Do not use

If an allergic reaction occurs, please stop using the product immediately and rinse thoroughly with plenty of water.

When Using

Use after cleansing the skin.

Stop Use

If an allergic reaction occurs, please stop using the product immediately and rinse thoroughly with plenty of water.

Ask Doctor

If an allergic reaction occurs, please stop using the product immediately and rinse thoroughly with plenty of water.

Keep Out Of Reach Of Children

For medical use only. Keep out of reach of children.

Directions

Use after cleansing the skin.

Other information

Store at room temperature or refrigerated. Keep the container sealed. Avoid high temperature, humidity and direct sunlight.

Inactive ingredients

SUNFLOWER OIL